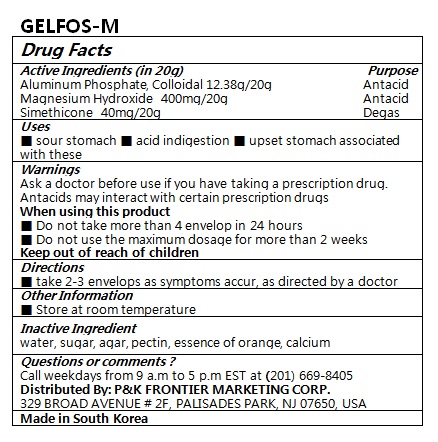 DRUG LABEL: GELFOS-M
NDC: 72988-0017 | Form: LIQUID
Manufacturer: LYDIA Co., Ltd
Category: otc | Type: HUMAN OTC DRUG LABEL
Date: 20191008

ACTIVE INGREDIENTS: ALUMINUM PHOSPHATE 12.38 g/20 g; MAGNESIUM HYDROXIDE 400 mg/20 g; DIMETHICONE 40 mg/20 g
INACTIVE INGREDIENTS: PECTIN; WATER; AGAR

ACTIVE INGREDIENT

Aluminum Phosphate, Colloidal

Magnesium Hydroxide

Simethicone

PURPOSE

■ sour stomach ■ acid indigestion ■ upset stomach associated with these

Keep out of reach of children

INDICATIONS AND USAGE

■ take 2-3 envelops as symptoms accur, as directed by a doctor

Warnings

Ask a doctor before use if you have taking a prescription drug. Antacids may interact with certain prescription drugs

When using this product

■ Do not take more than 4 envelop in 24 hours

■ Do not use the maximum dosage for more than 2 weeks

INACTIVE INGREDIENT

water, sugar, agar, pectin, essence of orange, calcium

DOSAGE AND ADMINISTRATION

For oral use only